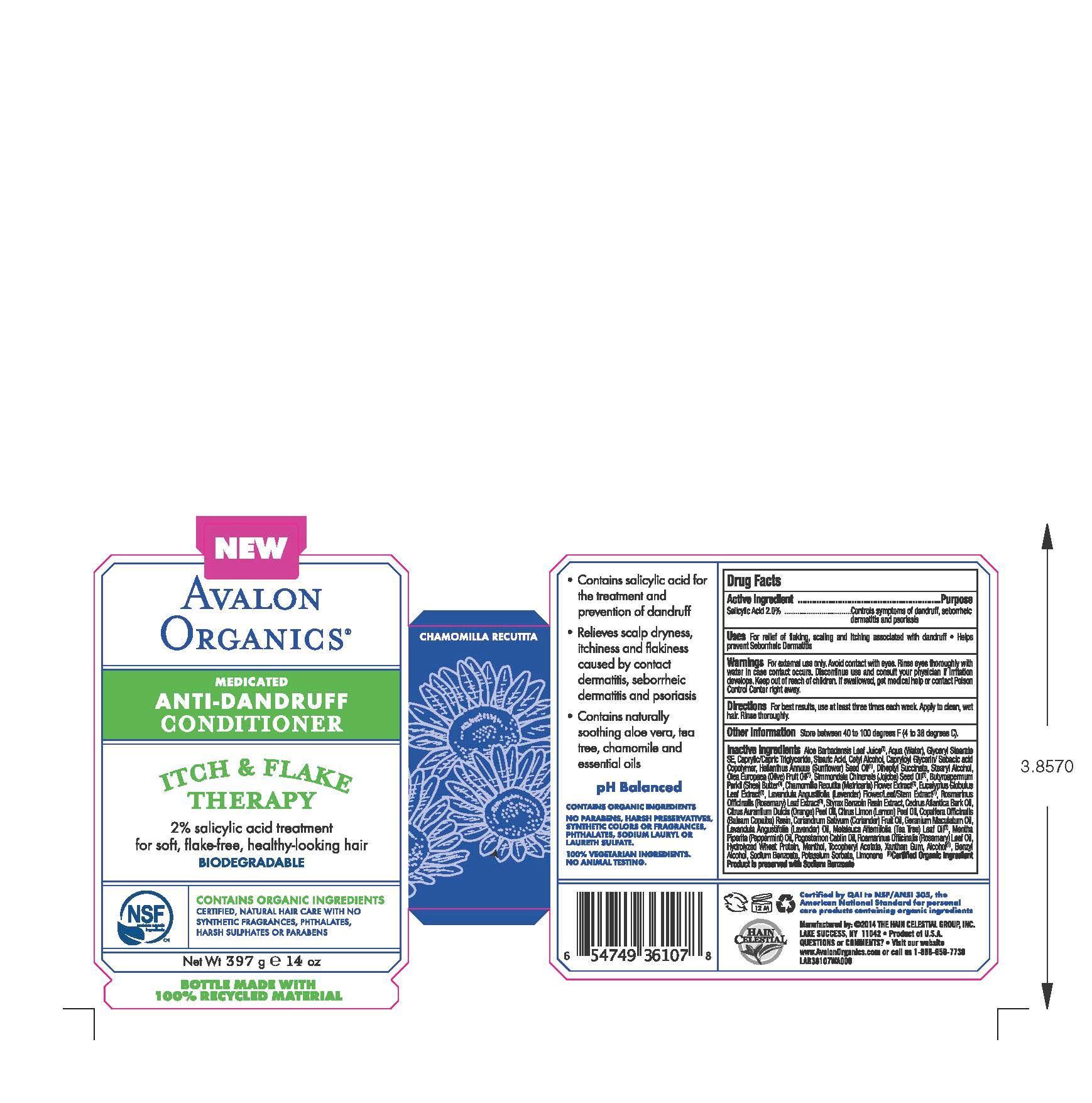 DRUG LABEL: Anti Dandruff
NDC: 61995-1107 | Form: RINSE
Manufacturer: The Hain Celestial Group, Inc.
Category: otc | Type: HUMAN OTC DRUG LABEL
Date: 20140204

ACTIVE INGREDIENTS: SALICYLIC ACID 2.0 g/397 g
INACTIVE INGREDIENTS: ALOE VERA LEAF; WATER; GLYCERYL STEARATE SE; CAPRYLIC/CAPRIC MONO/DIGLYCERIDES; STEARIC ACID; CETYL ALCOHOL; SUNFLOWER OIL; DIHEPTYL SUCCINATE; STEARYL ALCOHOL; OLIVE OIL; JOJOBA OIL; SHEA BUTTER; CHAMOMILE; EUCALYPTUS GLOBULUS LEAF; LAVANDULA ANGUSTIFOLIA FLOWER; MELALEUCA ALTERNIFOLIA LEAF; ROSMARINUS OFFICINALIS FLOWER; STYRAX BENZOIN RESIN; CEDRUS ATLANTICA BARK OIL; ORANGE OIL; LEMON OIL; COPAIFERA OFFICINALIS RESIN; CORIANDER OIL; GERANIUM MACULATUM WHOLE; LAVENDER OIL; MENTHA PIPERITA; POGOSTEMON CABLIN WHOLE; ROSEMARY OIL; .ALPHA.-BISABOLOL, (+)-; DISODIUM COCOYL GLUTAMATE; HYDROLYZED WHEAT PROTEIN (ENZYMATIC, 3000 MW); MENTHOL; .ALPHA.-TOCOPHEROL ACETATE; XANTHAN GUM; ALCOHOL; BENZYL ALCOHOL; POTASSIUM SORBATE; SODIUM BENZOATE

WARNINGS

For external use only. Avoid contact with eyes. Rinse eyes throughly with water in case contact ossurs. Discontinue to use and contact your physician if irritation develops.

Drug Facts

Salicylic Acid 2.0%

PURPOSE

Controls symptoms of dandruff, seboric dermatitis and psoriasis

Keep out of reach of children. If swallowed, get medical help or contact Poison Control Center right away.

INDICATIONS AND USAGE

For relief of flaking, scaling and itching associated with dandruff. Helps prevent Seborrheic Dermatitis

DOSAGE AND ADMINISTRATION

For the best results use at least three times each week. Apply to clean, wet hair. Rinse throughly.

INACTIVE INGREDIENT

Aloe Barbadensis Leaf Juice (1), Aqua (Water), Glyceryl Stearate SE, Caprylic/Capric Triglyceride, Stearic Acid,Cetyl Alcohol, Capryloyl Glycerin/Sebacic Acid Copolymer, Helianthus Annuus (Sunflower Seed Oi (1), Diheptyl Succinate, Stearyl Alcohol, Olea Europaea (Olive) Fruit Oil (1l, Simmondsia Chinensis (Jojoba) Seed Oil (1), Butyrospermum Parkii (Shea) Butter (1), Chamomilla Recuitita (Matricaria) Flower Extract (1), Eucalyptus Globulus Leaf Extract (1), Lavandula Angustifolia (Lavender) Flower/Leaf/Stem Extract (1), Rosmarinus Officinalis (Rosemmary) Leaf Extract (1), Styrax Benzoin Resin Extract, Malaleuca Alternifolia (Tea Tree) Leaf Oil (1), Rosmarinus Officinalis (Rosemary) Leaf Oil , Cedrus Atlantica Bark Oil, Citrus Aurantium Dulcis (Orange Peel Oil, Citrus Limon (Lemon) Peel Oil, Copaifera Officinalis (Balsam Copaiba) Resin, Coriandrum Sativum (Coriander) Fruit Oil, Geranium Maculatum Oil, Lavandula Angustifolia (Lavender) Oil, Mentha Piperita (Peppermint) Oil, Pogostemon Cablin Oil, Rosmarinus Officinalis (Rosemary) Leaf Oil, Hydrolyzed Wheat Protein, Menthol, Tocopheryl Acetate, Xanthan Gum, Alcohol, Benzyl Alcohol, Sodium Benzoate, Potassium Sorbate

(1) Certified Organic Ingredients